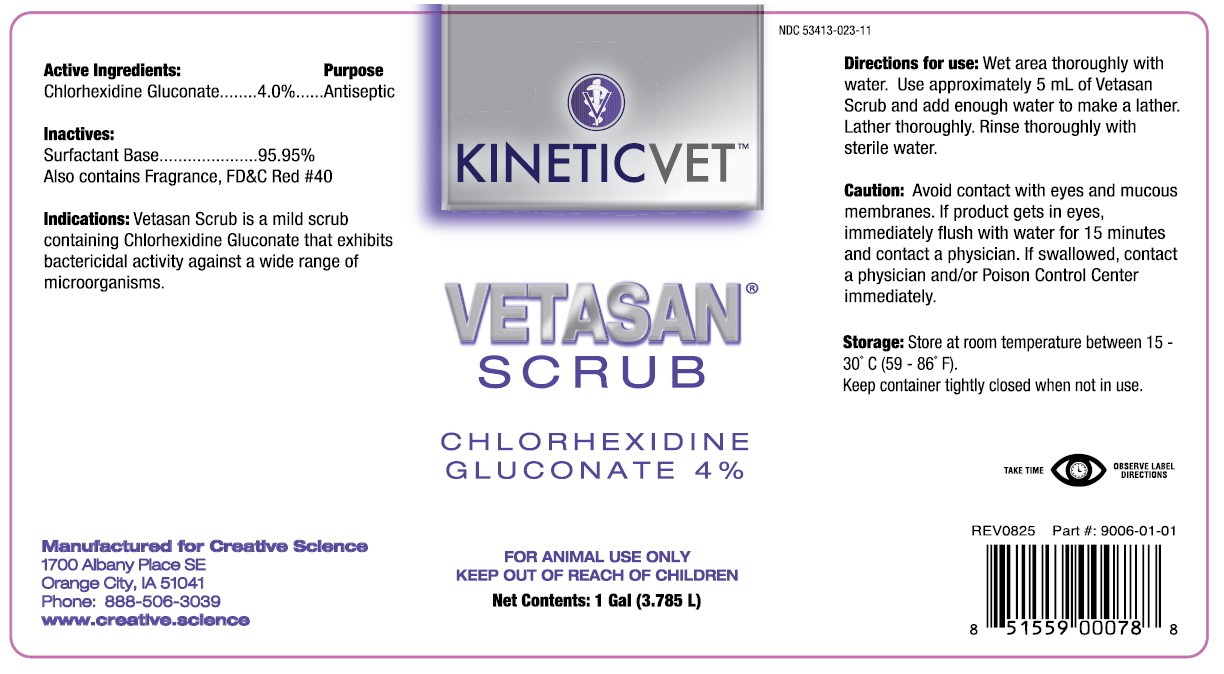 DRUG LABEL: VETASAN SCRUB
NDC: 53413-023 | Form: SOLUTION
Manufacturer: Creative Science
Category: animal | Type: OTC ANIMAL DRUG LABEL
Date: 20251231

ACTIVE INGREDIENTS: CHLORHEXIDINE GLUCONATE 4 g/0.1 L

VETASAN® SCRUB

Active Ingredients:

Chlorhexidine Gluconate........4.0%

Purpose

Antiseptic

Inactives:

Surfactant Base ....................... 95.95%

Also contains Fragrance, FD&C Red #40

Indications:

Vetasan Scrub is a mild scrub containing Chlorhexidine Gluconate that exhibits bactericidal activity against a wide range of microorganisms.

Manufactured for Creative Science

1700 Albany Place SE

Orange City, IA 51041

Phone: 888-506-3039

www.creative.science

NDC 53413-023-11

Directions for use:

Wet area thoroughly with water. Use approximately 5 mL of Vetasan Scrub and add enough water to make a lather. Lather thoroughly. Rinse thoroughly with sterile water.

Caution:

Avoid contact with eyes and mucous membranes. If product gets in eyes, immediately flush with water for 15 minutes and contact a physician. If swallowed, contact a physician and/or Poison Control Center immediately.

Storage:

Store at room temperature between 15 - 30°C (59 - 86°F).

Keep container tightly closed when not in use.

WARNINGS AND PRECAUTIONS

TAKE TIME OBSERVE LABEL DIRECTIONS

FOR ANIMAL USE ONLY

KEEP OUT OF REACH OF CHILDREN

REV0825 Part#: 9006-01-01

UPC 851559000788

PACKAGE LABEL

VETASAN® SCRUB

CHLORHEXIDINE GLUCONATE 4%

FOR ANIMAL USE ONLY

KEEP OUT OF REACH OF CHILDREN

Net Contents: 1 Gal (3.785 L)